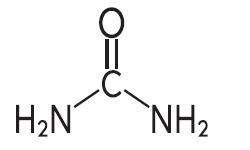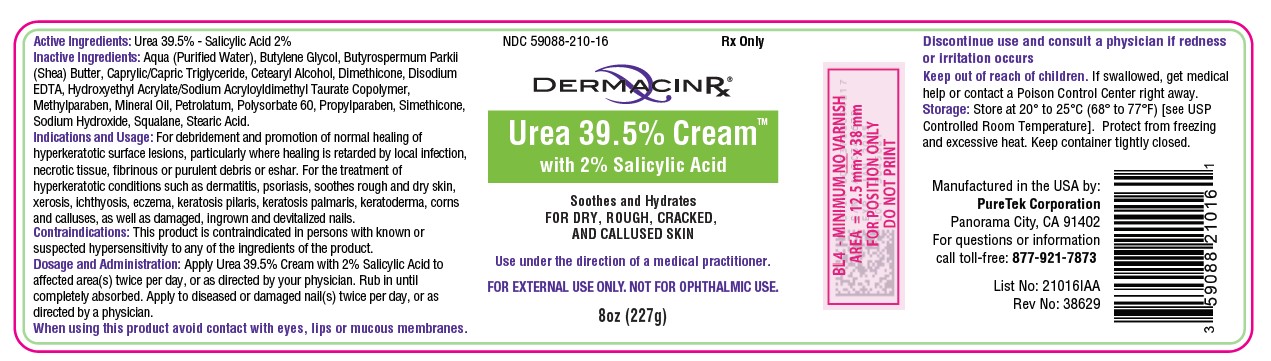 DRUG LABEL: Urea 39.5% with 2% Salicylic Acid
NDC: 59088-210 | Form: CREAM
Manufacturer: PureTek Corporation
Category: prescription | Type: HUMAN PRESCRIPTION DRUG LABEL
Date: 20230324

ACTIVE INGREDIENTS: UREA 39.5 g/100 g; SALICYLIC ACID 2 g/100 g
INACTIVE INGREDIENTS: BUTYLENE GLYCOL; SHEA BUTTER; MEDIUM-CHAIN TRIGLYCERIDES; CETOSTEARYL ALCOHOL; SODIUM HYDROXIDE; STEARIC ACID; EDETATE DISODIUM ANHYDROUS; METHYLPARABEN; WATER; HYDROXYETHYL ACRYLATE/SODIUM ACRYLOYLDIMETHYL TAURATE COPOLYMER (45000 MPA.S AT 1%); MINERAL OIL; PETROLATUM; PROPYLPARABEN; DIMETHICONE; SILICON DIOXIDE; SQUALANE; POLYSORBATE 60

Urea 39.5% Cream with 2% Salicylic Acid

DESCRIPTION

Urea 39.5% Cream with 2% Salicylic Acid is a keratolytic emollient which is a gentle, yet potent, tissue softener for nails and/or skin space. Each gram contains 395 mg of urea, 20 mg of Salicylic Acid in vehicle consisting of: Aqua (Purified Water), Butylene Glycol, Butyrospermum Parkii (Shea) Butter, Caprylic/Capric Triglyceride, Cetearyl Alcohol, Dimethicone, Disodium EDTA, Hydroxyethyl Acrylate/Sodium Acryloyldimethyl Taurate Copolymer, Methylparaben, Mineral Oil, Petrolatum, Polysorbate 60, Propylparaben, Simethicone, Sodium Hydroxide, Squalane, Stearic Acid.

Urea is a diamide of carbonic acid with the following chemical structure:

CLINICAL PHARMACOLOGY

Urea gently dissolves the intracellular matrix which results in loosening of the horny layer of the skin and shedding of scaly skin at regular intervals, thereby softening hyperkeratotic areas of the skin.

Pharmacokinetics

The mechanism of action of topically applied urea is not yet known.

INDICATIONS & USAGE

For debridement and promotion of normal healing of hyperkeratotic surface lesions, particularly where healing is retarded by local infection, necrotic tissue, fibrinous or purulent debris or eshar. Urea is useful for the treatment of hyperkeratotic conditions such as dermatitis, psoriasis, soothes rough and dry skin, xerosis, ichthyosis, eczema, keratosis pilaris, keratosis palmaris, keratoderma, corns and calluses, as well as damaged, ingrown and devitalized nails.

CONTRAINDICATIONS

This product is contraindicated in persons with known or suspected hypersensitivity to any of the ingredients of the product.

WARNINGS

FOREXTERNALUSEONLY. NOTFOR OPHTHALMIC USE. KEEP OUT OF REACH OF CHILDREN.

Avoid contact with eyes, lips and mucous membranes.When using this product skin irritation and dryness is more likely to occur.

General

This product is to be used as directed by a physician and should not be used to treat any condition other than that for which it was prescribed. If redness or irritation occurs, discontinue use and consult a physician.

Information for Patients

Patients should discontinue the use of this product if the condition becomes worse or if a rash develops in the area being treated or elsewhere. Avoid contact with eyes, lips and mucous membranes.

Carcinogenesis, Mutagenesis and Impairment of Fertility:

Long-term animal studies for carcinogenic potential have not been performed on this product to date. Studies on reproduction and fertility also have not been performed.

Pregnancy:

Category C. Animal reproduction studies have not been conducted with this product. It is also not known whether this product can affect reproduction capacity or cause fetal harm when administered to a pregnant woman. This product should be used by a pregnant woman only if clearly needed or when potential benefits outweigh potential hazards to the fetus.

Nursing Mothers:

It is not known whether this drug is excreted in human milk. Because many drugs are excreted in human milk, caution should be exercised when this product is administered to a nursing woman.

ADVERSE REACTIONS:

Transient stinging, burning, itching or irritation may occur and normally disappear upon discontinuing the medication.

DOSAGE AND ADMINISTRATION

Apply Urea 39.5% Cream with 2% Salicylic Acid to affected skin twice per day, or as directed by your physician. Rub in until completely absorbed.
Apply to diseased or damaged nail(s) twice per day, or as directed by a physician.

HOW SUPPLIED

Urea 39.5% Cream with 2% Salicylic Acid 8 oz. (227 g): NDC 59088-210-16

STORAGE

Store at 20° to 25°C (68° to 77°F) [see USP Controlled Room Temperature]. Protect from freezing and excessive heat. Keep container tightly closed.

KEEP THIS AND ALL MEDICATIONS OUT OF THE REACH OF CHILDREN.

Urea 39.5% Cream™ with 2% Salicylic Acid

Manufactured in the USA by:
PureTek Corporation
Panorama City, CA 91402
For questions or information
call toll-free: 877-921-7873